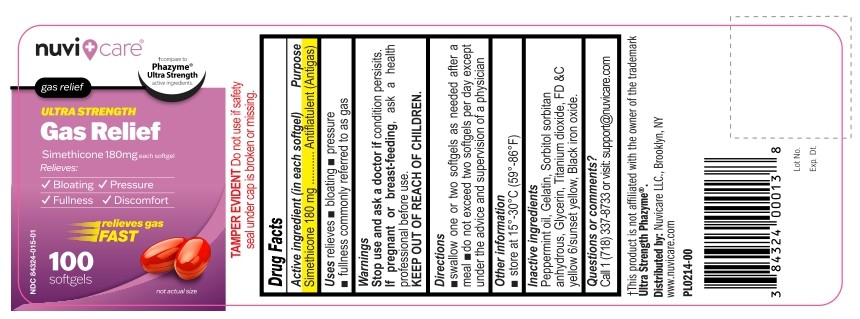 DRUG LABEL: Gas Relief Simethicone 180mg Softgel
NDC: 84324-015 | Form: CAPSULE, LIQUID FILLED
Manufacturer: NUVICARE LLC
Category: otc | Type: HUMAN OTC DRUG LABEL
Date: 20251219

ACTIVE INGREDIENTS: DIMETHICONE 180 mg/1 1
INACTIVE INGREDIENTS: PEPPERMINT OIL; GELATIN; SORBITOL; SORBITAN; GLYCERIN; FD&C YELLOW NO. 6; TITANIUM DIOXIDE; FERROSOFERRIC OXIDE

Gas Relief Simethicone 180mg Softgel

Active Ingredient (in each softgel)

Simethicone 180 mg

Purpose

Antiflatulent (Antigas)

Uses

relieves

- bloating
- pressure
- fullness commonly referred to as gas

Warnings

Stop use and ask a doctor if condition persists.

If pregnant or breast-feeding, ask a health professional before use.

KEEP OUT OF REACH OF CHILDREN.

Directions

- swallow one or two softgels as needed after a meal
- do not exceed two softgels per day except under the advice and supervision of a physician

Other Information

- store at 15° to 30°C (59° to 86°F)

Inactive Ingredients

Peppermint oil, Gelatin, Sorbitol, sorbitan anhydrous, Glycerin, Titanium dioxide, FD &C yellow 6/sunset yellow, Black iron oxide.

Questions or Comments?

Call 1 (718) 337-8733 or visit support@nuvicare.com